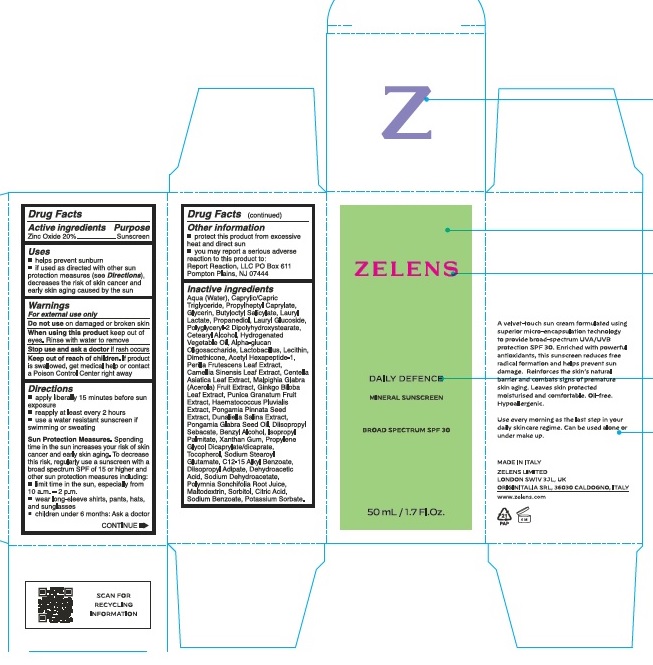 DRUG LABEL: Zelens Daily Defence Mineral Sunscreen SPF 30
NDC: 63712-001 | Form: CREAM
Manufacturer: Zelens Limited
Category: otc | Type: HUMAN OTC DRUG LABEL
Date: 20230519

ACTIVE INGREDIENTS: ZINC OXIDE 200 mg/1 mL
INACTIVE INGREDIENTS: BUTYLOCTYL SALICYLATE; PONGAMIA PINNATA SEED; LAURYL LACTATE; DUNALIELLA SALINA; MALPIGHIA GLABRA FRUIT; SODIUM STEAROYL GLUTAMATE; ACETYL HEXAPEPTIDE-1; POMEGRANATE; BENZYL ALCOHOL; MEDIUM-CHAIN TRIGLYCERIDES; DIISOPROPYL SEBACATE; CENTELLA ASIATICA LEAF; GINKGO; XANTHAN GUM; PROPYLENE GLYCOL DICAPRYLATE/DICAPRATE; PROPYLHEPTYL CAPRYLATE; DIMETHICONE; DIISOPROPYL ADIPATE; .ALPHA.-GLUCAN OLIGOSACCHARIDE; LECITHIN, SOYBEAN; PROPANEDIOL; POLYGLYCERYL-2 DIPOLYHYDROXYSTEARATE; GLYCERIN; GREEN TEA LEAF; MALTODEXTRIN; SORBITOL; CITRIC ACID MONOHYDRATE; TOCOPHEROL; SODIUM DEHYDROACETATE; SODIUM BENZOATE; DEHYDROACETIC ACID; WATER; LAURYL GLUCOSIDE; CETOSTEARYL ALCOHOL; POTASSIUM SORBATE; PERILLA FRUTESCENS LEAF; HAEMATOCOCCUS PLUVIALIS; KARUM SEED OIL; ISOPROPYL PALMITATE; ALKYL (C12-15) BENZOATE; SMALLANTHUS SONCHIFOLIUS ROOT JUICE

Zelens Daily Defence Mineral Sunscreen SPF 30

Active ingredients

Zinc Oxide 20%

Purpose

Sunscreen

Uses

- helps prevent sunburn
- if used as directed with other sun protection measures (see Directions), decreases the risk of skin cancer and early skin aging caused by the sun

Warnings

For external use only

Do not use

on damaged or broken skin

Wen using this product

keep out of eyes. Rinse with water to remove

Stop use and ask a doctor

if rash occurs

Keep out of reach of children.

If product is swallowed, get medical help or contact a Poison Control Center right away

Directions

- apply liberally 15 minutes before sun exposure
- reapply at least every 2 hours
- use a water resistant sunscreen if swimming or sweating

Sun Protection Measures. Spending time in the sun increases your risk of skin cancer and early skin aging. To decrease this risk, regularly use a sunscreen with a broad spectrum SPF of 15 or higher and other sun protection measures including:

- limit time in the sun, especially from 10 a.m. - 2 p.m.
- wear long-sleeve shirts, pants, hats and sunglasses
- children under 6 months: Ask a doctor

Other information

- protect this product from excessive heat and direct sun
- you may report a serious adverse reaction to this product to: Report Reaction, LLC PO Box 611 Pompton Plains, NJ 07444

Inactive ingredients

Aqua (Water), Caprylic/Capric Triglyceride, Propylheptyl Caprylate, Glycerin, Butyloctyl Salicylate, Lauryl Lactate, Propanediol, Lauryl Glucoside, Polyglyceryl-2 Dipolyhydroxystearate, Cetearyl Alcohol, Hydrogenated Vegetable Oil, Alpha-glucan Oligosaccharide, Lactobacillus, Lecithin, Dimethicone, Acetyl Hexapeptide-1 Perilla Frutescens Leaf Extract, Camellia Sinensis Leaf Extract, Centella Asiatica Leaf Extract, Malpighia Glabra (Acerola) Fruit Extract, Ginkgo Biloba Leaf Extract, Punica Granatum Fruit Extract, Haematococcus Pluvialis Extract, Pongamia Pinnata Seed Extract, Dunliella Salina Extract, Pongamia Glabra Seed Oil, Diisopropyl Sebacate, Benzyl Alcohol, Isopropyl Palmitate, Xanthan Gum, Propylene Glycol Dicaprylate/dicaprate, Tocopherol, Sodium Stearoyl Glutamate, C12-15 Alkyl Benzoate, Diisopropyl Adipate, Dehydroacetic Acid, Sodium Dehydroacetate, Polymnia Sonchifolia Root Juice, Maltodextrin, Sorbitol, Citric Acid, Sodium Benzoate, Potassium Sorbate.

Company Information

ZELENS LIMITED

LONDON SW1V 3JL, UK

www.zelens.com